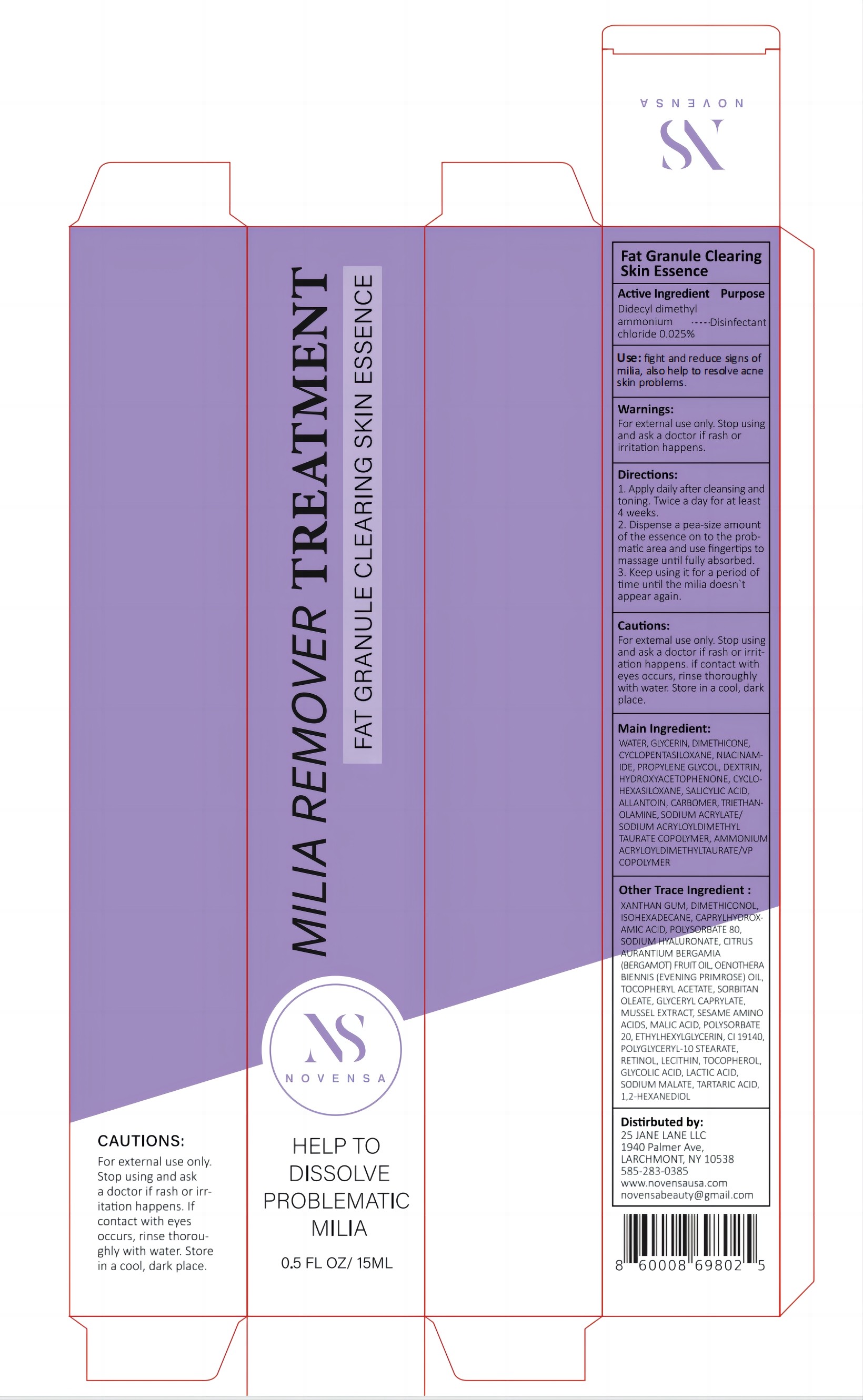 DRUG LABEL: Milia Remover Treatment
NDC: 83818-001 | Form: LIQUID
Manufacturer: Shenzhen Xinxin Yunhai Technology Co., Ltd.
Category: otc | Type: HUMAN OTC DRUG LABEL
Date: 20250104

ACTIVE INGREDIENTS: SALICYLIC ACID 0.15 g/100 mL; DIDECYLDIMONIUM CHLORIDE 0.025 g/100 mL; NIACINAMIDE 0.5 g/100 mL
INACTIVE INGREDIENTS: DIMETHICONE; CYCLOMETHICONE 5; PROPYLENE GLYCOL; CYCLOMETHICONE 6; ALLANTOIN; HYDROXYACETOPHENONE

83818-001 Update

Active Ingredient

Didecyl Dimethyl Ammonium Chloride 0.025%

Salicylic Acid 0.15%

NIACINAMIDE 0.5%

Purpose

Fat grandule clearing Skin essence

Use

to fight and reduce signs of milia

Warnings

For external use only

Keep away from fire and flame

Do not use

if rash or irritation happens

When Using

Do not apply on other parts of the body

Avoid contact with eyes. In case of accidental contact, rinse eyes with a large amount of cool tap water

Stop Use

if rash or irritation happens

Ask Doctor

When Pregnant or breast-feeding

Keep Oot Of Reach Of Children

Directions

Slide the essence on the promatic area and use fingertips to massage until fully absorbed.

Other information

Before use, read all information on the carton

Inactive ingredients

DIMETHICONE,CYCLOPENTASILOXANE,PROPYLENE GLYCOL,HYDROXYACETOPHENONE,CYCLOHEXASILOXANE,ALLANTOIN

Questions

novensabeauty@gmail.com